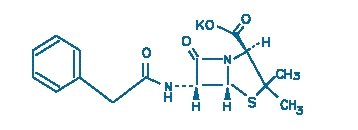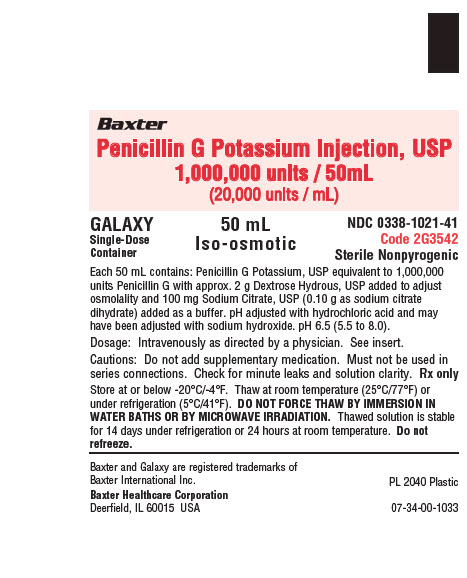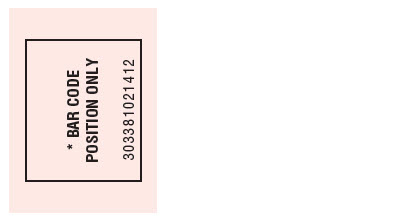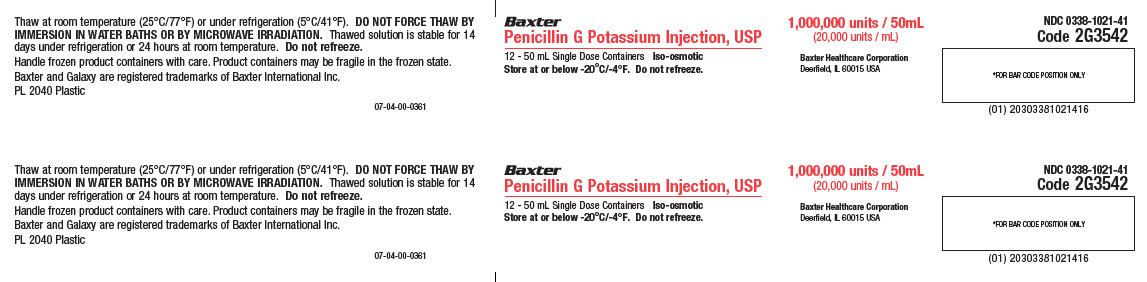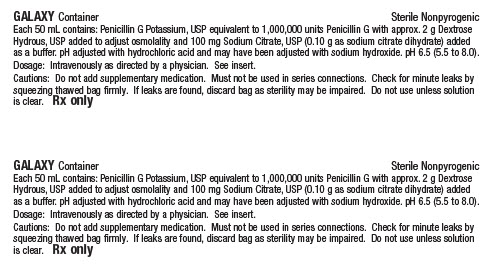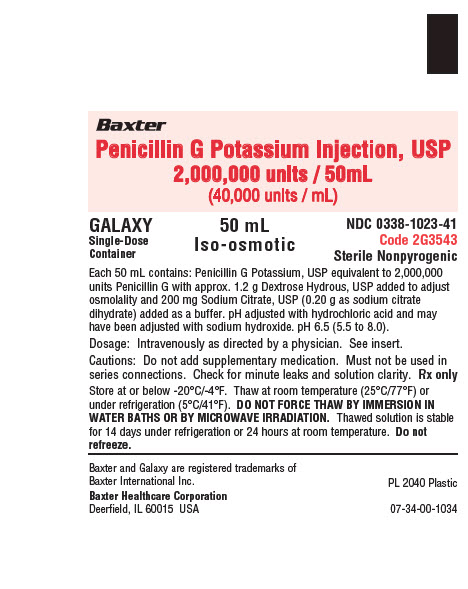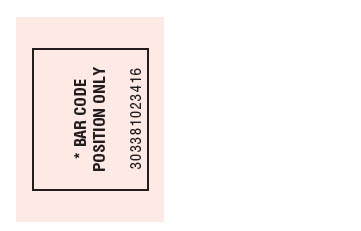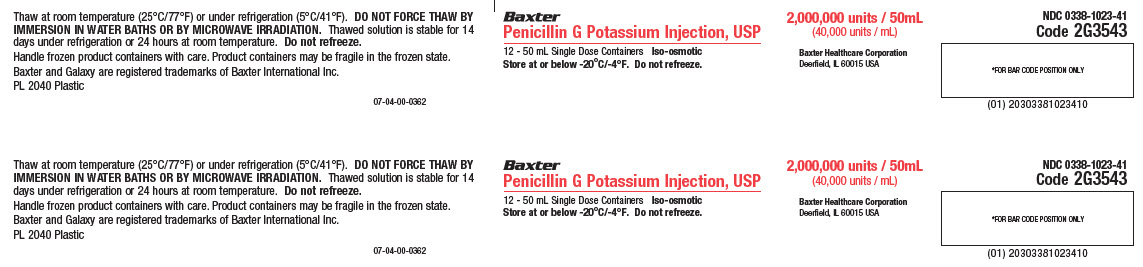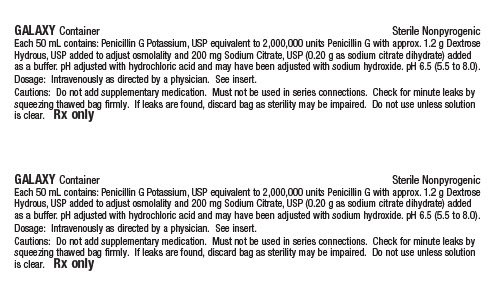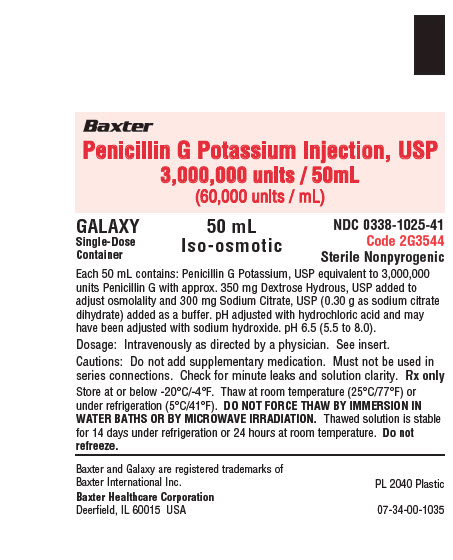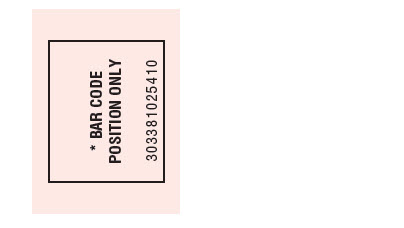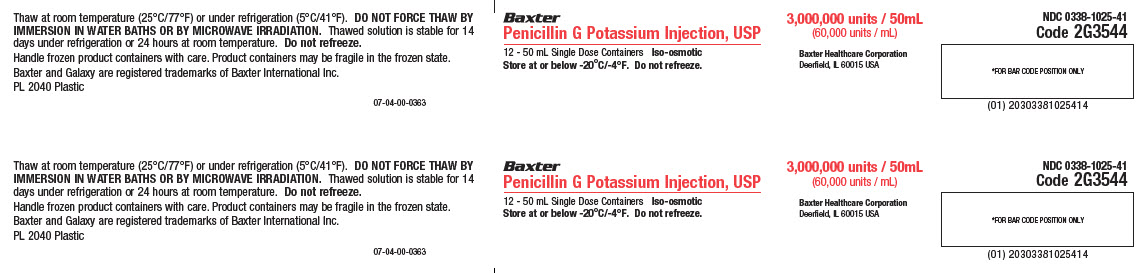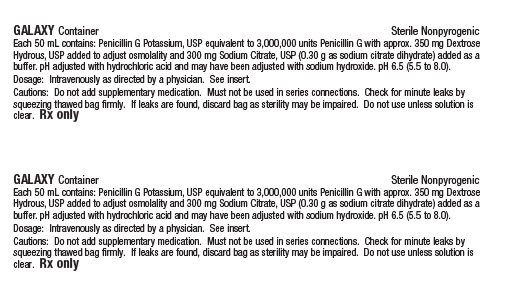 DRUG LABEL: PENICILLIN G POTASSIUM
NDC: 0338-1025 | Form: INJECTION, SOLUTION
Manufacturer: Baxter Healthcare Corporation
Category: prescription | Type: HUMAN PRESCRIPTION DRUG LABEL
Date: 20210513

ACTIVE INGREDIENTS: PENICILLIN G POTASSIUM 3000000 [iU]/50 mL
INACTIVE INGREDIENTS: DEXTROSE MONOHYDRATE 350 mg/50 mL; TRISODIUM CITRATE DIHYDRATE 300 mg/50 mL; HYDROCHLORIC ACID; SODIUM HYDROXIDE; WATER

Penicillin G Potassium
Injection, USP
In PL 2040 Plastic Container
For Intravenous Use Only
GALAXY Container (PL 2040 Plastic)

To reduce the development of drug-resistant bacteria and maintain the effectiveness of Penicillin G Potassium Injection, USP and other antibacterial drugs, Penicillin G Potassium Injection, USP should be used only to treat or prevent infections that are proven or strongly suspected to be caused by bacteria.

DESCRIPTION

Penicillin G Potassium, USP is a natural penicillin. It is chemically designated 4-Thia-1-azabicyclo[3.2.0]heptane-2-carboxylic acid,3,3-dimethyl-7-oxo-6-[(phenylacetyl)amino]-, monopotassium salt, [2S-(2α, 5α, 6β)]. It is crystalline. It is freely soluble in water, in isotonic sodium chloride solution and in dextrose solutions. The structural formula is as shown below.

Penicillin G Potassium Injection, USP (equivalent to 1, 2, or 3 million units of penicillin G) is a 50 mL premixed, iso-osmotic, sterile, nonpyrogenic, frozen solution for intravenous administration. Dextrose, USP has been added to the above dosages to adjust osmolality (approximately 2 g, 1.2 g, and 350 mg as dextrose hydrous, respectively). Sodium Citrate, USP has been added as a buffer (0.10 g, 0.20 g and 0.30 g as sodium citrate dihydrate, respectively). The pH has been adjusted with hydrochloric acid and may have been adjusted with sodium hydroxide. The pH is 6.5 (5.5 to 8.0). The solution is contained in a single dose GALAXY container (PL 2040 Plastic) and is intended for intravenous use after thawing to room temperature.

This GALAXY container is fabricated from a specially designed multilayer plastic (PL 2040). Solutions are in contact with the polyethylene layer of this container and can leach out certain chemical components of the plastic in very small amounts within the expiration period. The suitability of the plastic has been confirmed in tests in animals according to the USP biological tests for plastic containers as well as by tissue culture toxicity studies.

CLINICAL PHARMACOLOGY

After an intravenous infusion of penicillin G, peak serum concentrations are attained immediately after completion of the infusion. In a study of ten patients administered a single 5 million unit dose of penicillin G intravenously over 3-5 minutes, the mean serum concentrations were 400 mcg/mL, 273 mcg/mL and 3.0 mcg/mL at 5-6 minutes, 10 minutes and 4 hours after completion of the injection, respectively. In a separate study, five healthy adults were administered one million units of penicillin G intravenously, either as a bolus over 4 minutes or as an infusion over 60 minutes. The mean serum concentration eight minutes after completion of the bolus was 45 mcg/mL and eight minutes after completion of the infusion was 14.4 mcg/mL. The mean β-phase serum half-life of penicillin G administered by the intravenous route in ten patients with normal renal function was 42 minutes, with a range of 31-50 minutes.

The clearance of penicillin G in normal individuals is predominantly via the kidney. The renal clearance, which is extremely rapid, is the result of glomerular filtration and active tubular transport, with the latter route predominating. Urinary recovery is reported to be 58-85% of the administered dose. Renal clearance of penicillin is delayed in premature infants, neonates and in the elderly due to decreased renal function. The serum half-life of penicillin G correlates inversely with age and clearance of creatinine and ranges from 3.2 hours in infants 0 to 6 days of age to 1.4 hours in infants 14 days of age or older.

Nonrenal clearance includes hepatic metabolism and, to a lesser extent, biliary excretion. The latter routes become more important with renal impairment.

Probenecid blocks the renal tubular secretion of penicillin. Therefore, the concurrent administration of probenecid prolongs the elimination of penicillin G and, consequently, increases the serum concentrations.

Penicillin G is distributed to most areas of the body including lung, liver, kidney, muscle, bone and placenta. In the presence of inflammation, levels of penicillin in abscesses, middle ear, pleural, peritoneal and synovial fluids are sufficient to inhibit most susceptible bacteria. Penetration into the eye, brain, cerebrospinal fluid (CSF) or prostate is poor in the absence of inflammation. With inflamed meninges, the penetration of penicillin G into the CSF improves, such that the CSF/serum ratio is 2-6%. Inflammation also enhances its penetration into the pericardial fluid. Penicillin G is actively secreted into the bile resulting in levels at least 10 times those achieved simultaneously in serum. Penicillin G penetrates poorly into human polymorphonuclear leukocytes.

In the presence of impaired renal function, the β-phase serum half-life of penicillin G is prolonged. β-phase serum half-lives of one to two hours were observed in azotemic patients with serum creatinine concentrations <3 mg/100 mL and ranged as high as 20 hours in anuric patients. A linear relationship, including the lowest range of renal function, is found between the serum elimination rate constant and renal function as measured by creatinine clearance.

In patients with altered renal function, the presence of hepatic insufficiency further alters the elimination of penicillin G. In one study, the serum half-lives in two anuric patients (excreting <400 mL urine/day) were 7.2 and 10.1 hours. A totally anuric patient with terminal hepatic cirrhosis had a penicillin half-life of 30.5 hours, while another patient with anuria and liver disease had a serum half-life of 16.4 hours. The dosage of penicillin G should be reduced in patients with severe renal impairment, with additional modifications when hepatic disease accompanies the renal impairment. Hemodialysis has been shown to reduce penicillin G serum levels.

Microbiology

Penicillin G is bactericidal against penicillin-susceptible microorganisms during the stage of active multiplication. It acts by inhibiting biosynthesis of cell-wall mucopeptide. It is not active against the penicillinase-producing bacteria, which include many strains of staphylococci. Penicillin G is highly active in vitro against staphylococci (except penicillinase-producing strains), streptococci (groups A, B, C, G, H, L and M), pneumococci and Neisseria meningitidis.

Other organisms susceptible in vitro to penicillin G are Neisseria gonorrhoeae, Corynebacterium diphtheriae, Bacillus anthracis, clostridia, Actinomyces species, Spirillum minus, Streptobacillus moniliformis, Listeria monocytogenes, and leptospira; Treponema pallidum is extremely susceptible. Some species of gram-negative bacilli were previously considered susceptible to very high intravenous doses of penicillin G (up to 80 million units/day) including some strains of Escherichia coli, Proteus mirabilis, salmonella, shigella, Enterobacter aerogenes (formerly Aerobacter aerogenes) and Alcaligenes faecalis. Penicillin G is no longer considered a drug of choice for infections caused by these organisms.

Susceptibility Test Methods

For specific information regarding susceptibility test interpretive criteria and associated test methods and quality control standards recognized by FDA for this drug, please see: http://www.fda.gov/STIC.

INDICATIONS AND USAGE

Therapy

Penicillin G Potassium Injection, USP is indicated in the treatment of serious infections caused by susceptible strains of the designated microorganisms in the conditions listed below. Appropriate culture and susceptibility tests should be done before treatment in order to isolate and identify organisms causing infection and to determine their susceptibility to penicillin G.
Therapy with Penicillin G Potassium Injection, USP may be initiated before results of such tests are known when there is reason to believe the infection may involve any of the organisms listed below; however, once these results become available, appropriate therapy should be continued.

CLINICAL INDICATION | INFECTING ORGANISM
Septicemia, empyema, pneumonia, pericarditis, endocarditis, meningitis | Streptococcus pyogenes (group A β-hemolytic streptococcus), other β-hemolytic streptococci including groups C, H, G, L and M, Streptococcus pneumoniae and Staphylococcus species (non-penicillinase producing strains)
Anthrax | Bacillus anthracis
Actinomycosis (cervico-facial disease and thoracic and abdominal disease) | Actinomyces israelii
Botulism (adjunctive therapy to antitoxin), gas gangrene, and tetanus (adjunctive therapy to human tetanus immune globulin) | Clostridium species
Diphtheria (adjunctive therapy to antitoxin and prevention of the carrier state) | Corynebacterium diphtheriae
Erysipelothrix endocarditis | Erysipelothrix rhusiopathiae
Fusospirochetosis (severe infections of the oropharynx [Vincent’s], lower respiratory tract and genital area) | Fusobacterium species and spirochetes
Listeria infections including meningitis and endocarditis | Listeria monocytogenes
Pasteurella infections including bacteremia and meningitis | Pasteurella multocida
Haverhill fever | Streptobacillus moniliformis
Rat bite fever | Spirillum minus or Streptobacillus moniliformis
Disseminated gonococcal infections | Neisseria gonorrhoeae (penicillin-susceptible)
Syphilis (congenital and neurosyphilis) | Treponema pallidum
Meningococcal meningitis and/or septicemia | Neisseria meningitidis
Gram-negative bacillary infections (bacteremias) Penicillin G is not the drug of choice in the treatment of gram-negative bacillary infections. | Gram-negative bacillary organisms (i.e. Enterobacteriaceae)

To reduce the development of drug-resistant bacteria and maintain the effectiveness of Penicillin G Potassium Injection, USP and other antibacterial drugs, Penicillin G Potassium Injection, USP should be used only to treat or prevent infections that are proven or strongly suspected to be caused by susceptible bacteria. When culture and susceptibility information are available, they should be considered in selecting or modifying antibacterial therapy. In the absence of such data, local epidemiology and susceptibility patterns may contribute to the empiric selection of therapy.

CONTRAINDICATIONS

A history of a hypersensitivity (anaphylactic) reaction to any penicillin is a contraindication. Solutions containing dextrose may be contraindicated in patients with known allergy to corn or corn products.

WARNINGS

Serious and occasionally fatal hypersensitivity (anaphylactic) reactions have been reported in patients on penicillin therapy. These reactions are more likely to occur in individuals with a history of penicillin hypersensitivity and/or a history of sensitivity to multiple allergens. There have been reports of individuals with a history of penicillin hypersensitivity who have experienced severe reactions when treated with cephalosporins. Before initiating therapy with penicillin G, careful inquiry should be made concerning previous hypersensitivity reactions to penicillins, cephalosporins, or other allergens. If an allergic reaction occurs, penicillin G should be discontinued and appropriate therapy instituted. Serious anaphylactic reactions require immediate emergency treatment with epinephrine. Oxygen, intravenous steroids, and airway management, including intubation, should also be administered as indicated.

Clostridium difficile associated diarrhea (CDAD) has been reported with use of nearly all antibacterial agents, including Penicillin G Potassium Injection, USP, and may range in severity from mild diarrhea to fatal colitis. Treatment with antibacterial agents alters the normal flora of the colon leading to overgrowth of C. difficile.

C. difficile produces toxins A and B which contribute to the development of CDAD. Hypertoxin producing strains of C. difficile cause increased morbidity and mortality, as these infections can be refractory to antimicrobial therapy and may require colectomy. CDAD must be considered in all patients who present with diarrhea following antibiotic use. Careful medical history is necessary since CDAD has been reported to occur over two months after the administration of antibacterial agents.

If CDAD is suspected or confirmed, ongoing antibiotic use not directed against C. difficile may need to be discontinued. Appropriate fluid and electrolyte management, protein supplementation, antibiotic treatment of C. difficile, and surgical evaluation should be instituted as clinically indicated.

PRECAUTIONS

General

Penicillin should be used with caution in individuals with histories of significant allergies and/or asthma (see WARNINGS). Whenever allergic reactions occur, penicillin should be withdrawn unless, in the opinion of the physician, the condition being treated is life-threatening and amenable only to penicillin therapy. Penicillin G Potassium, USP by the intravenous route in high doses (above 10 million units) should be administered slowly because of the potential adverse effects of electrolyte imbalance from the potassium content of the penicillin. Penicillin G Potassium Injection, USP contains 1.7 mEq potassium and 1.02 mEq of sodium per million units. The use of antibiotics may promote overgrowth of nonsusceptible organisms, including fungi. Indwelling intravenous catheters encourage superinfections. Should superinfection occur, appropriate measures should be taken. When indicated, incision and drainage or other surgical procedures should be performed in conjunction with antibiotic therapy.

Prescribing Penicillin G Potassium Injection, USP in the absence of a proven or strongly suspected bacterial infection or a prophylactic indication is unlikely to provide benefit to the patient and increases the risk of the development of drug-resistant bacteria.

Laboratory Tests

Periodic assessment of organ system function, including frequent evaluation of electrolyte balance, hepatic, renal and hematopoietic systems, and cardiac and vascular status should be performed during prolonged therapy with high doses of intravenous penicillin G (see ADVERSE REACTIONS). If any impairment of function is suspected or known to exist, a reduction in the total dosage should be considered (see DOSAGE AND ADMINISTRATION). In suspected staphylococcal infections, proper laboratory studies, including susceptibility tests should be performed. All infections due to Group A beta-hemolytic streptococci should be treated for at least 10 days.

Patients being treated for gonococcal infection should have a serologic test for syphilis before receiving penicillin. All cases of penicillin treated syphilis should receive adequate follow-up including clinical and serological examinations. The recommended follow-up varies with the stage of syphilis being treated.

Drug Interactions

Bacteriostatic antibacterials (i.e., chloramphenicol, erythromycins, sulfonamides or tetracyclines) may antagonize the bactericidal effect of penicillin, and concurrent use of these drugs should be avoided. This has been documented in vitro; however, the clinical significance of this interaction is not well-documented.

Penicillin blood levels may be prolonged by concurrent administration of probenecid which blocks the renal tubular secretion of penicillins. Other drugs may compete with penicillin G for renal tubular secretion and thus prolong the serum half-life of penicillin. These drugs include: aspirin, phenylbutazone, sulfonamides, indomethacin, thiazide diuretics, furosemide and ethacrynic acid.

Drug/Laboratory Test Interactions

After treatment with penicillin G, a false-positive reaction for glucose in the urine may occur with Benedict’s solution, Fehling’s solution or CLINITEST tablet, but not with the enzyme-based tests, such as CLINISTIX and TES-TAPE.

Penicillin G has been associated with pseudoproteinuria by certain test methods.

Carcinogenesis, Mutagenesis, Impairment of Fertility

No long term animal studies have been conducted with this drug.

Pregnancy

Reproduction studies performed in the mouse, rat and rabbit have revealed no evidence of impaired fertility or harm to the fetus due to penicillin G. Human experience with the penicillins during pregnancy has not shown any positive evidence of adverse effects on the fetus. There are, however, no adequate and well controlled studies in pregnant women showing conclusively that harmful effects of these drugs on the fetus can be excluded. Because animal reproduction studies are not always predictive of human response, this drug should be used during pregnancy only if clearly needed.

Nursing Mothers

Penicillins are excreted in human milk. Caution should be exercised when penicillins are administered to a nursing woman.

Pediatric Use

Incompletely developed renal function in newborns may delay elimination of penicillin; therefore, appropriate reductions in the dosage and frequency of administration should be made in these patients. All newborns treated with penicillins should be monitored closely for clinical and laboratory evidence of toxic or adverse effects (see PRECAUTIONS).

Pediatric doses are generally determined on a weight basis and should be calculated for each patient individually. Recommended guidelines for pediatric dosages are presented in Dosage and Administration.

The potential for toxic effects in children from chemicals that may leach from the single dose premixed intravenous preparation in plastic containers has not been evaluated.

Geriatric Use

Clinical studies of Penicillin G Injection did not include sufficient numbers of subjects aged 65 and over to determine whether they respond differently from younger subjects. Other reported clinical experience has not identified differences in responses between the elderly and younger patients. In general, dose selection for an elderly patient should be cautious, usually starting at the low end of the dosing range, reflecting the greater frequency of decreased hepatic, renal, or cardiac function, and of concomitant disease or other drug therapy.

This drug is known to be substantially excreted by the kidney, and the risk of toxic reactions to this drug may be greater in patients with impaired renal function. Because elderly patients are more likely to have decreased renal function, care should be taken in dose selection, and it may be useful to monitor renal function.

Penicillin G Injection contains 23.5 mg (1.02 mEq) of sodium per million units. At the usual recommended doses, patients would receive between 23.5 and 564 mg/day (1.02 and 24.5 mEq) of sodium. The geriatric population may respond with a blunted natriuresis to salt loading. This may be clinically important with regard to such diseases as congestive heart failure.

Information for Patients

Patients should be counseled that antibacterial drugs including Penicillin G Potassium Injection, USP should only be used to treat bacterial infections. They do not treat viral infections (e.g., the common cold). When Penicillin G Potassium Injection, USP is prescribed to treat a bacterial infection, patients should be told that although it is common to feel better early in the course of therapy, the medication should be taken exactly as directed. Skipping doses or not completing the full course of therapy may (1) decrease the effectiveness of the immediate treatment and (2) increase the likelihood that bacteria will develop resistance and will not be treatable by Penicillin G Potassium Injection, USP or other antibacterial drugs in the future.

Diarrhea is a common problem caused by antibiotics which usually ends when the antibiotic is discontinued. Sometimes after starting treatment with antibiotics, patients can develop watery and bloody stools (with or without stomach cramps and fever) even as late as two or more months after having taken the last dose of the antibiotic. If this occurs, patients should contact their physician as soon as possible.

ADVERSE REACTIONS

Body as a whole: The Jarisch-Herxheimer reaction is a systemic reaction, that may occur after the initiation of penicillin therapy in patients with syphilis or other spirochetal infections (i.e., Lyme disease and Relapsing fever). The reaction begins one to two hours after initiation of therapy and disappears within 12 to 24 hours. It is characterized by fever, chills, myalgias, headache, exacerbation of cutaneous lesions, tachycardia, hyperventilation, vasodilation with flushing and mild hypotension. The pathogenesis of the Herxheimer reaction may be due to the release from the spirochetes of heat-stable pyrogen.

Hypersensitivity reactions: The reported incidence of allergic reactions to all penicillins ranges from 0.7 to 10 percent in different studies (see WARNINGS). Sensitization is usually the result of previous treatment with a penicillin, but some individuals have had immediate reactions when first treated. In such cases, it is postulated that prior exposure to penicillin may have occurred via trace amounts present in milk or vaccines.

Two types of allergic reactions to penicillin are noted clinically - immediate and delayed. Immediate reactions usually occur within 20 minutes of administration and range in severity from urticaria and pruritus to angioneurotic edema, laryngospasm, bronchospasm, hypotension, vascular collapse and death (see WARNINGS). Such immediate anaphylactic reactions are very rare and usually occur after parenteral therapy, but a few cases of anaphylaxis have been reported following oral therapy. Another type of immediate reaction, an accelerated reaction, may occur between 20 minutes and 48 hours after administration and may include urticaria, pruritus, fever and, occasionally, laryngeal edema.

Delayed reactions to penicillin therapy usually occur within 1-2 weeks after initiation of therapy. Manifestations include serum sickness-like symptoms, i.e., fever, malaise, urticaria, myalgia, arthralgia, abdominal pain and various skin rashes, ranging from maculopapular eruptions to exfoliative dermatitis.

Contact dermatitis has been observed in individuals who prepare penicillin solutions.

Gastrointestinal system: Pseudomembranous colitis has been reported with the onset occurring during or after penicillin G treatment. Nausea, vomiting, stomatitis, black or hairy tongue, and other symptoms of gastrointestinal irritation may occur, especially during oral therapy.

Hematologic system: Reactions include neutropenia, which resolves after penicillin therapy is discontinued; Coombs-positive hemolytic anemia, an uncommon reaction, occurs in patients treated with intravenous penicillin G in doses greater than 10 million units/day and who have previously received large doses of the drug; and with large doses of penicillin, a bleeding diathesis can occur secondary to platelet dysfunction.

Metabolic: Penicillin G Potassium, USP (1 million units contains 1.7 mEq of potassium ion) may cause serious and even fatal electrolyte disturbances, i.e., hyperkalemia, when given intravenously in large doses.

Nervous system: Neurotoxic reactions including hyperreflexia, myoclonic twitches, seizures and coma have been reported following the administration of massive intravenous doses, and are more likely in patients with impaired renal function.

Urogenital system: Renal tubular damage and interstitial nephritis have been associated with large intravenous doses of penicillin G. Manifestations of this reaction may include fever, rash, eosinophilia, proteinuria, eosinophiluria, hematuria and a rise in serum urea nitrogen. Discontinuation of penicillin G results in resolution in the majority of patients.

Local reactions: Phlebitis and thrombophlebitis may occur, and pain at the injection site has been reported with intravenous administration.

OVERDOSAGE

Dose related toxicity may arise with the use of massive doses of intravenous penicillins (40 to 100 million units per day), particularly in patients with severe renal impairment (see PRECAUTIONS). The manifestations may include agitation, confusion, asterixis, hallucinations, stupor, coma, multifocal myoclonus, seizures and encephalopathy. Hyperkalemia is also possible (see ADVERSE REACTIONS-Metabolic).

In case of overdosage, discontinue penicillin, treat symptomatically and institute supportive measures as required. If necessary, hemodialysis may be used to reduce blood levels of Penicillin G, although the degree of effectiveness of this procedure is questionable.

DOSAGE AND ADMINISTRATION

Penicillin G Potassium Injection, USP should be administered by intravenous infusion. The usual dose recommendations are as follows:

Adult patients

(*) Because of its short half-life, Penicillin G is administered in divided doses, usually
every 4-6 hours with the exception of meningococcal meningitis/septicemia, i.e., every 2 hours.

CLINICAL INDICATION | DOSAGE
Serious infections due to susceptible strains of streptococci (including S. pneumoniae) -septicemia, empyema, pneumonia, pericarditis, endocarditis and meningitis | 12 to 24 million units/day depending on the infection and its severity administered in equally divided doses every 4-6 hours.
Serious infections due to susceptible strains of staphylococci - septicemia, empyema, pneumonia, pericarditis, endocarditis and meningitis | 5 to 24 million units/day depending on the infection and its severity administered in equally divided doses every 4-6 hours.
Anthrax | Minimum of 8 million units/day in divided doses every 6 hours. Higher doses may be required depending on susceptibility of organism.
Actinomycosis Cervicofacial disease Thoracic and abdominal disease | 1 to 6 million units/day(*) 10 to 20 million units/day(*)
Clostridial infections Botulism (adjunctive therapy to antitoxin) Gas gangrene (debridement and/or surgery as indicated) Tetanus (adjunctive therapy to human tetanus immune globulin) | 20 million units/day(*)
Diphtheria (adjunctive therapy to antitoxin and for the prevention of the carrier state) | 2 to 3 million units/day in divided doses for 10-12 days(*)
Erysipelothrix endocarditis | 12 to 20 million units/day for 4-6 weeks(*)
Fusospirochetosis (severe infections of the oropharynx [Vincent’s], lower respiratory tract and genital area) | 5 to 10 million units/day(*)
Listeria infections Meningitis Endocarditis | 15 to 20 million units/day for 2 weeks(*) 15 to 20 million units/day for 4 weeks(*)
Pasteurella infections including bacteremia and meningitis | 4 to 6 million units/day for 2 weeks(*)
Haverhill fever; Rat-bite fever | 12 to 20 million units/day for 3-4 weeks(*)
Disseminated gonococcal infections, such as meningitis endocarditis, arthritis, etc., caused by penicillin - susceptible organisms | 10 million units/day(*); duration depends on the type of infection
Syphilis (neurosyphilis) | 12 to 24 million units/day, as 2-4 MU every 4 hours for 10-14 days; many experts recommend additional therapy with Benzathine PCN G 2.4 MU IM weekly for 3 doses after completion of IV therapy
Meningococcal meningitis and/or septicemia | 24 million units/day as 2 million units every 2 hours

Pediatric patients

This product should not be administered to patients requiring less than one million units per dose

(see PRECAUTIONS-Pediatric Use).

CLINICAL INDICATION | DOSAGE
Serious infections, such as pneumonia and endocarditis, due to susceptible strains of streptococci (including S. pneumoniae) and meningococcus | 150,000–300,000 units/kg/day divided in equal doses every 4-6 hours; duration depends on infecting organism and type of infection
Meningitis caused by susceptible strains of pneumococcus and meningococcus | 250,000 units/kg/day divided in equal doses every 4 hours for 7-14 days depending on the infecting organism (maximum dose of 12-20 million units/day)
Disseminated Gonococcal Infections (penicillin-susceptible strains) | Weight less than 45 kg:
Arthritis | 100,000 units/kg/day in 4 equally divided doses for 7-10 days
Meningitis | 250,000 units/kg/day in equal doses every 4 hours for 10-14 days
Endocarditis | 250,000 units/kg/day in equal doses every 4 hours for 4 weeks
Arthritis, meningitis, endocarditis | Weight 45 kg or greater: 10 million units/day in 4 equally divided doses with the duration of therapy depending on the type of infection
Syphilis (congenital and neurosyphilis) after the newborn period | 200,000-300,000 units/kg/day (administered as 50,000 units/kg every 4-6 hours) for 10-14 days
Diphtheria (adjunctive therapy to antitoxin and for prevention of the carrier state) | 150,000-250,000 units/kg/day in equal doses every 6 hours for 7-10 days
Rat-bite fever; Haverhill fever (with endocarditis caused by S. moniliformis) | 150,000-250,000 units/kg/day in equal doses every 4 hours for 4 weeks

Renal Impairment: Penicillin G is relatively nontoxic, and dosage adjustments are generally required only in cases of severe renal impairment. The recommended dosage regimens are as follows:

Creatinine clearance less than 10 mL/min/1.73m^2; administer a full loading dose (see recommended dosages in the tables above) followed by one-half of the loading dose every 8-10 hours.

Uremic patients with a creatinine clearance greater than 10 mL/min/1.73m^2; administer a full loading dose (see recommended dosages in the tables above) followed by one-half of the loading dose every 4-5 hours. Additional dosage modifications should be made in patients with hepatic disease and renal impairment.

For most acute infections, treatment should be continued for at least 48 to 72 hours after the patient becomes asymptomatic. Antibiotic therapy for Group A β-hemolytic streptococcal infections should be maintained for at least 10 days to reduce the risk of rheumatic fever. Parenteral drug products should be inspected visually for particulate matter and discoloration prior to administration whenever solution and container permit.

DIRECTIONS FOR USE OF GALAXY CONTAINER (PL 2040 PLASTIC)

Penicillin G Potassium Injection, USP in GALAXY Container (PL 2040 Plastic) is for intravenous administration using sterile equipment.

Storage

Store in a freezer capable of maintaining a temperature of -20°C/-4°F.

Thawing of Plastic Container

Thaw frozen container at room temperature (25°C/77°F) or in a refrigerator (5°C/41°F). DO NOT FORCE THAW BY IMMERSION IN WATER BATHS OR BY MICROWAVE IRRADIATION.

Check for minute leaks by squeezing container firmly. If leaks are detected, discard solution as sterility may be impaired.

Do not add supplementary medication.

Visually inspect the container. If the outlet port protector is damaged, detached, or not present, discard container as solution path sterility may be impaired. Components of the solution may precipitate in the frozen state and will dissolve upon reaching room temperature with little or no agitation. Potency is not affected. Agitate after solution has reached room temperature. If after visual inspection the solution remains cloudy or if an insoluble precipitate is noted, or if any seals are not intact, the container should be discarded. The thawed solution is stable for 14 days under refrigeration (5°C/41°F) or for 24 hours at room temperature (25°C/77°F). Do not refreeze thawed antibiotics.

CAUTION: Do not use plastic containers in series connections. Such use could result in air embolism due to residual air being drawn from the primary container before administration of the fluid from the secondary container is complete.

Preparation for Intravenous Administration:

1. Suspend container from eyelet support.
2. Remove protector from outlet port at bottom of container.
3. Attach administration set. Refer to complete directions accompanying set.

HOW SUPPLIED/STORAGE AND HANDLING

Penicillin G Potassium Injection, USP is supplied as a premixed frozen iso-osmotic solution in 50 mL single dose GALAXY containers (PL 2040 Plastic) as follows:

2G3542 | NDC 0338-1021-41 | 1,000,000 units/50 mL (20,000 units/mL) Penicillin G
2G3543 | NDC 0338-1023-41 | 2,000,000 units/50 mL (40,000 units/mL) Penicillin G
2G3544 | NDC-0338-1025-41 | 3,000,000 units/50 mL (60,000 units/mL) Penicillin G

Store at or below -20°C/-4°F. [See DIRECTIONS FOR USE OF GALAXY CONTAINER (PL 2040 Plastic).]

Handle frozen product containers with care. Product containers may be fragile in the frozen state.

Baxter Healthcare Corporation
Deerfield, IL 60015 USA

Printed in USA

Baxter and Galaxy are registered trademarks of Baxter International Inc.

Clinistix is a registered trademark of Ascensia Diabetes Care Holdings AG

Clinitest is a trademark of Siemens Healthcare Diagnostics Inc.

07-19-03-154

Rev. May 2021

PRINCIPAL DISPLAY PANEL - PACKAGING LABELING

Container Label

Baxter Logo

Penicillin G Potassium Injection, USP
1,000,000 units/ 50mL
(20,000 units / mL)

GALAXY
Single-Dose
Container

50 mL
Iso-osmotic

NDC 0338-1021-41
Code 2G3542
Sterile Nonpyrogenic

Each 50 mL contains: Penicillin G Potassium, USP equivalent to 1,000,000
units Penicillin G with approx. 2 g Dextrose Hydrous, USP added to adjust
osmolality and 100 mg Sodium Citrate, USP (0.10 g as sodium citrate
dihydrate) added as a buffer. pH adjusted with hydrochloric acid and may
have been adjusted with sodium hydroxide. pH 6.5 (5.5 to 8.0).

Dosage: Intravenously as directed by a physician. See insert.
Cautions: Do not add supplementary medication. Must not be used in
series connections. Check for minute leaks and solution clarity. Rx only

Store at or below -20°C/-4°F. Thaw at room temperature (25°C/77°F) or
under refrigeration (5°C/41°F). DO NOT FORCE THAW BY IMMERSION IN
WATER BATHS OR BY MICROWAVE IRRADIATION. Thawed solution is stable
for 14 days under refrigeration or 24 hours at room temperature. Do not
refreeze.

Baxter and Galaxy are registered trademarks of
Baxter International Inc.

Baxter Healthcare Corporation
Deerfield, IL 60015 USA

PL 2040 Plastic
07-34-00-1033

*BAR CODE
POSITION ONLY

303381021412

Carton Label

Thaw at room temperature (25°C/77°F) or under refrigeration (5°C/41°F). DO NOT FORCE THAW BY IMMERSION IN WATER BATHS OR BY MICROWAVE IRRADIATION. Thawed solution is stable for 14 days under refrigeration or 24 hours at room temperature. Do not refreeze.

Handle frozen product containers with care. Product containers may be fragile in the frozen state.
Baxter and Galaxy are registered trademarks of Baxter International Inc.
PL 2040 Plastic

07-04-00-0361

Baxter Logo

Penicillin G Potassium Injection, USP
12 - 50 mL Single Dose Containers Iso-osmotic
Store at or below -20°C/-4°F. Do not refreeze.

1,000,000 units / 50mL
(20,000 units / mL)

Baxter Healthcare Corporation
Deerfield, IL 60015 USA

NDC 0338-1021-41
Code 2G3542

*FOR BAR CODE POSITION ONLY
(01) 20303381021416

GALAXY Container
Sterile Nonpyrogenic

Each 50 mL contains: Penicillin G Potassium, USP equivalent to 1,000,000 units Penicillin G with approx. 2 g Dextrose Hydrous, USP added to adjust osmolality and 100 mg Sodium Citrate, USP (0.10 g as sodium citrate dihydrate) added as a buffer. pH adjusted with hydrochloric acid and may have been adjusted with sodium hydroxide. pH 6.5 (5.5 to 8.0).

Dosage: Intravenously as directed by a physician. See insert.

Cautions: Do not add supplementary medication. Must not be used in series connections. Check for minute leaks by squeezing thawed bag firmly. If leaks are found, discard bag as sterility may be impaired. Do not use unless solution is clear. Rx only

Container Label

Baxter Logo

Penicillin G Potassium Injection, USP
2,000,000 units / 50mL
(40,000 units / mL)

GALAXY
Single-Dose
Container

50 mL
Iso-osmotic

NDC 0338-1023-41
Code 2G3543
Sterile Nonpyrogenic

Each 50 mL contains: Penicillin G Potassium, USP equivalent to 2,000,000
units Penicillin G with approx. 1.2 g Dextrose Hydrous, USP added to adjust
osmolality and 200 mg Sodium Citrate, USP (0.20 g as sodium citrate
dihydrate) added as a buffer. pH adjusted with hydrochloric acid and may
have been adjusted with sodium hydroxide. pH 6.5 (5.5 to 8.0).

Dosage: Intravenously as directed by a physician. See insert.

Cautions: Do not add supplementary medication. Must not be used in
series connections. Check for minute leaks and solution clarity. Rx only
Store at or below -20°C/-4°F. Thaw at room temperature (25°C/77°F) or
under refrigeration (5°C/41°F). DO NOT FORCE THAW BY IMMERSION IN
WATER BATHS OR BY MICROWAVE IRRADIATION. Thawed solution is stable
for 14 days under refrigeration or 24 hours at room temperature. Do not
refreeze.

Baxter and Galaxy are registered trademarks of
Baxter International Inc.

Baxter Healthcare Corporation
Deerfield, IL 60015 USA

PL 2040 Plastic
07-34-00-1034

*BAR CODE
POSITION ONLY

303381023416

Carton Label

Thaw at room temperature (25°C/77°F) or under refrigeration (5°C/41°F). DO NOT FORCE THAW BY IMMERSION IN WATER BATHS OR BY MICROWAVE IRRADIATION. Thawed solution is stable for 14 days under refrigeration or 24 hours at room temperature. Do not refreeze.

Handle frozen product containers with care. Product containers may be fragile in the frozen state.
Baxter and Galaxy are registered trademarks of Baxter International Inc.
PL 2040 Plastic

07-04-00-0362

Baxter Logo

Penicillin G Potassium Injection, USP
12 - 50 mL Single Dose Containers Iso-osmotic
Store at or below -20°C/-4°F. Do not refreeze.

2,000,000 units / 50mL
(40,000 units / mL)

Baxter Healthcare Corporation
Deerfield, IL 60015 USA

NDC 0338-1023-41
Code 2G3543

*FOR BAR CODE POSITION ONLY
(01) 20303381023410

GALAXY Container
Sterile Nonpyrogenic

Each 50 mL contains: Penicillin G Potassium, USP equivalent to 2,000,000 units Penicillin G with approx. 1.2 g Dextrose

Hydrous, USP added to adjust osmolality and 200 mg Sodium Citrate, USP (0.20 g as sodium citrate dihydrate) added as a buffer. pH adjusted with hydrochloric acid and may have been adjusted with sodium hydroxide. pH 6.5 (5.5 to 8.0).

Dosage: Intravenously as directed by a physician. See insert.

Cautions: Do not add supplementary medication. Must not be used in series connections. Check for minute leaks by squeezing thawed bag firmly. If leaks are found, discard bag as sterility may be impaired. Do not use unless solution is clear. Rx only

Container Label

Baxter Logo

Penicillin G Potassium Injection, USP
3,000,000 units / 50mL
(60,000 units / mL)

GALAXY
Single-Dose
Container

50 mL
Iso-osmotic

NDC 0338-1025-41
Code 2G3544
Sterile Nonpyrogenic

Each 50 mL contains: Penicillin G Potassium, USP equivalent to 3,000,000
units Penicillin G with approx. 350 mg Dextrose Hydrous, USP added to
adjust osmolality and 300 mg Sodium Citrate, USP (0.30 g as sodium citrate
dihydrate) added as a buffer. pH adjusted with hydrochloric acid and may
have been adjusted with sodium hydroxide. pH 6.5 (5.5 to 8.0).

Dosage: Intravenously as directed by a physician. See insert.

Cautions: Do not add supplementary medication. Must not be used in
series connections. Check for minute leaks and solution clarity. Rx only

Store at or below -20°C/-4°F. Thaw at room temperature (25°C/77°F) or
under refrigeration (5°C/41°F). DO NOT FORCE THAW BY IMMERSION IN
WATER BATHS OR BY MICROWAVE IRRADIATION. Thawed solution is stable
for 14 days under refrigeration or 24 hours at room temperature. Do not
refreeze.

Baxter and Galaxy are registered trademarks of
Baxter International Inc.

Baxter Healthcare Corporation
Deerfield, IL 60015 USA

PL 2040 Plastic
07-34-00-1035

*BAR CODE
POSITION ONLY
303381025410

Carton Label

Thaw at room temperature (25°C/77°F) or under refrigeration (5°C/41°F). DO NOT FORCE THAW BY
IMMERSION IN WATER BATHS OR BY MICROWAVE IRRADIATION. Thawed solution is stable for 14 days under refrigeration or 24 hours at room temperature. Do not refreeze.

Handle frozen product containers with care. Product containers may be fragile in the frozen state.
Baxter and Galaxy are registered trademarks of Baxter International Inc.
PL 2040 Plastic

07-04-00-0363

Baxter Logo

Penicillin G Potassium Injection, USP
12 - 50 mL Single Dose Containers Iso-osmotic
Store at or below -20°C/-4°F. Do not refreeze.

3,000,000 units / 50mL
(60,000 units / mL)

Baxter Healthcare Corporation
Deerfield, IL 60015 USA

NDC 0338-1025-41
Code 2G3544

*FOR BAR CODE POSITION ONLY
(01) 20303381025414

GALAXY Container
Sterile Nonpyrogenic

Each 50 mL contains: Penicillin G Potassium, USP equivalent to 3,000,000 units Penicillin G with approx. 350 mg Dextrose Hydrous, USP added to adjust osmolality and 300 mg Sodium Citrate, USP (0.30 g as sodium citrate dihydrate) added as a buffer. pH adjusted with hydrochloric acid and may have been adjusted with sodium hydroxide. pH 6.5 (5.5 to 8.0).

Dosage: Intravenously as directed by a physician. See insert.

Cautions: Do not add supplementary medication. Must not be used in series connections. Check for minute leaks by squeezing thawed bag firmly. If leaks are found, discard bag as sterility may be impaired. Do not use unless solution is clear. Rx only